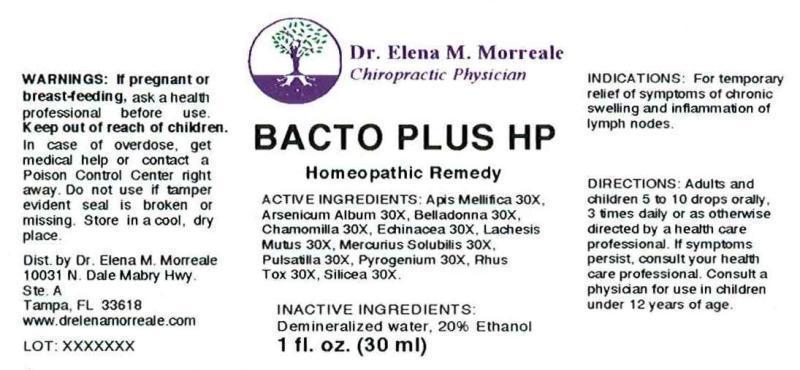 DRUG LABEL: BACTO PLUS HP
NDC: 50813-0010 | Form: LIQUID
Manufacturer: Dr. Elena M. Morreale, Chiropractic Life Center
Category: homeopathic | Type: HUMAN OTC DRUG LABEL
Date: 20141208

ACTIVE INGREDIENTS: APIS MELLIFERA 30 [hp_X]/1 mL; ARSENIC TRIOXIDE 30 [hp_X]/1 mL; ATROPA BELLADONNA 30 [hp_X]/1 mL; MATRICARIA RECUTITA 30 [hp_X]/1 mL; ECHINACEA ANGUSTIFOLIA 30 [hp_X]/1 mL; LACHESIS MUTA VENOM 30 [hp_X]/1 mL; MERCURIUS SOLUBILIS 30 [hp_X]/1 mL; PULSATILLA VULGARIS 30 [hp_X]/1 mL; RANCID BEEF 30 [hp_X]/1 mL; TOXICODENDRON PUBESCENS LEAF 30 [hp_X]/1 mL; SILICON DIOXIDE 30 [hp_X]/1 mL
INACTIVE INGREDIENTS: WATER; ALCOHOL

DRUG FACTS:

ACTIVE INGREDIENTS:

APIS MELLIFICA 30X, ARSENICUM ALBUM 30X, BELLADONNA 30X, CHAMOMILLA 30X, ECHINACEA (ANGUSTIFOLIA) 30X, LACHESIS MUTUS 30X, MERCURIUS SOLUBILIS 30X, PULSATILLA (VULGARIS) 30X, PYROGENIUM 30X, RHUS TOXICODENDRON 30X, SILICEA 30X

INDICATIONS:

For temporary relief of symptoms of chronic swelling and inflammation of lymph nodes.

WARNINGS:

If pregnant or breast-feeding, ask a health professional before use.

Keep out of reach of children. In case of overdose, get medical help or contact a Poison Control Center right away.

Do not use if tamper evident seal is broken or missing.

Store in a cool, dry place.

Keep out of reach of children. In case of overdose, get medical help or contact a Poison Control Center right away.

DIRECTIONS:

Adults and children 5 to 10 drops orally, 3 times daily or as otherwise directed by a healthcare professional. If symptoms persist, consult your health care professional. Consult a physician for use in children under 12 years of age.

INDICATIONS:

For temporary relief of symptoms of chronic swelling and inflammation of lymph nodes.

INACTIVE INGREDIENTS:

Demineralized Water, 20% Ethanol

QUESTIONS:

Dist. by Dr. Elena M. Morreale

10031 N. Dale Mabry Hwy.

Ste. A

Tampa, FL 33618

www.drelenamorreale.com

PACKAGE LABEL DISPLAY:

Dr. Elena M. Morreale

Chiropractic Physician

BACTO PLUS HP

Homeopathic Remedy

1 fl. oz. (30 ml)